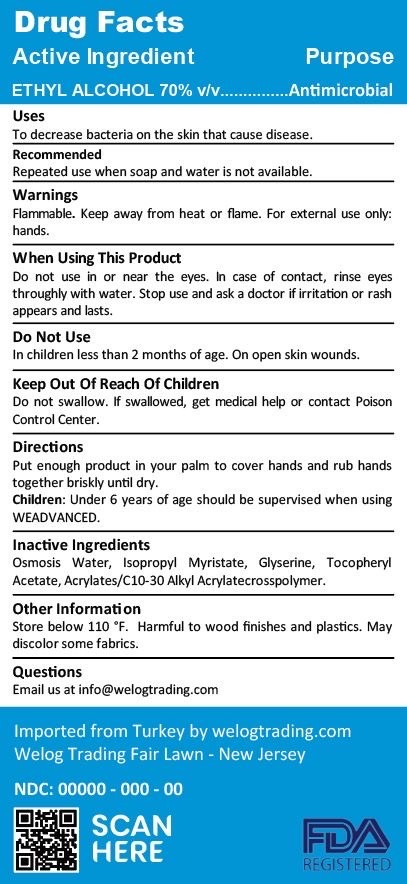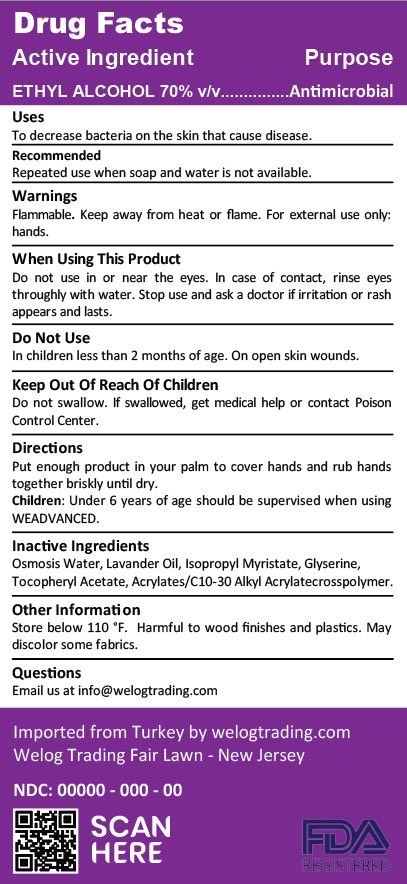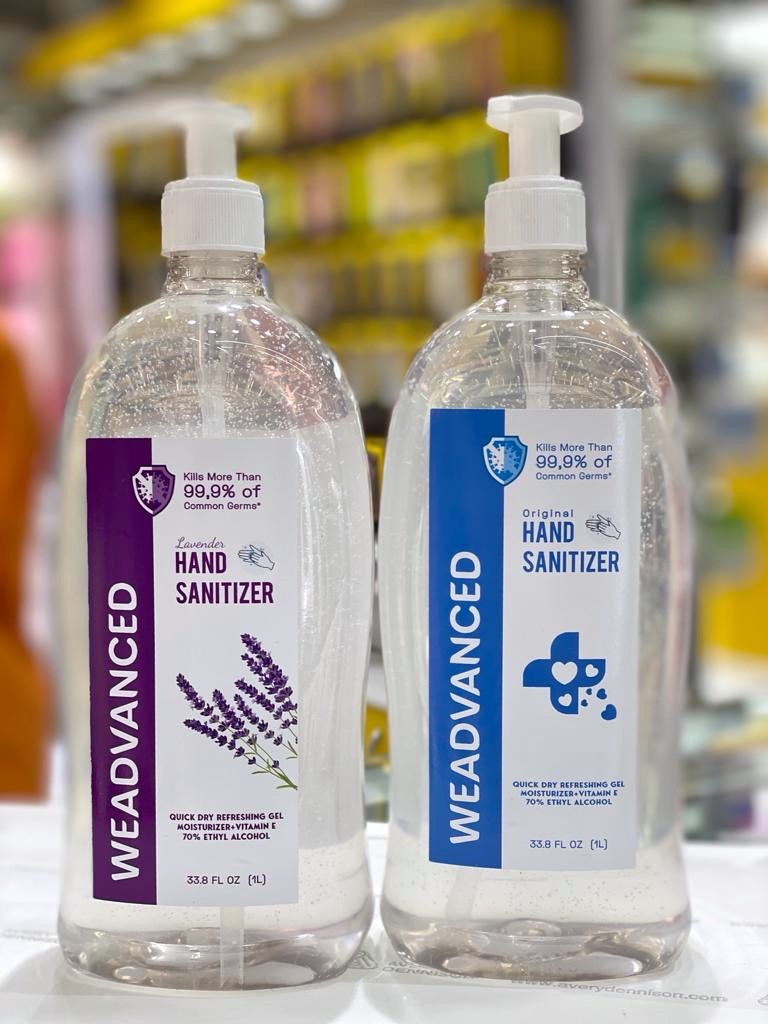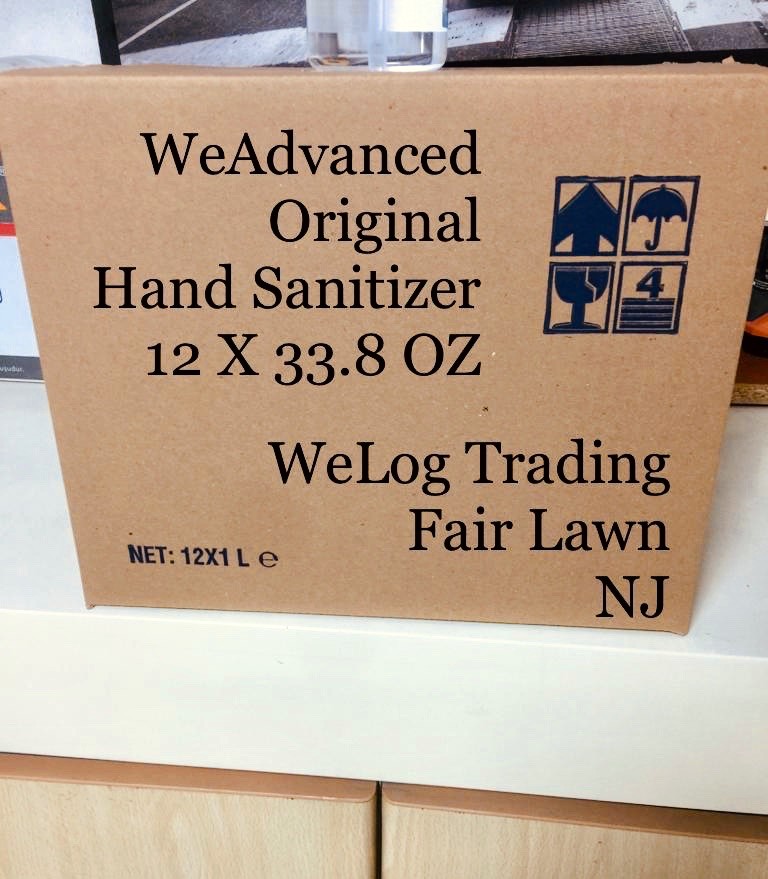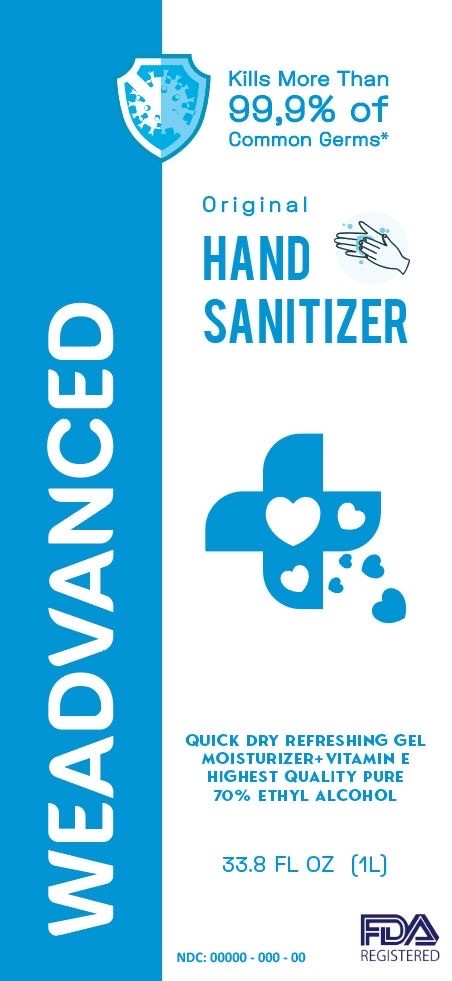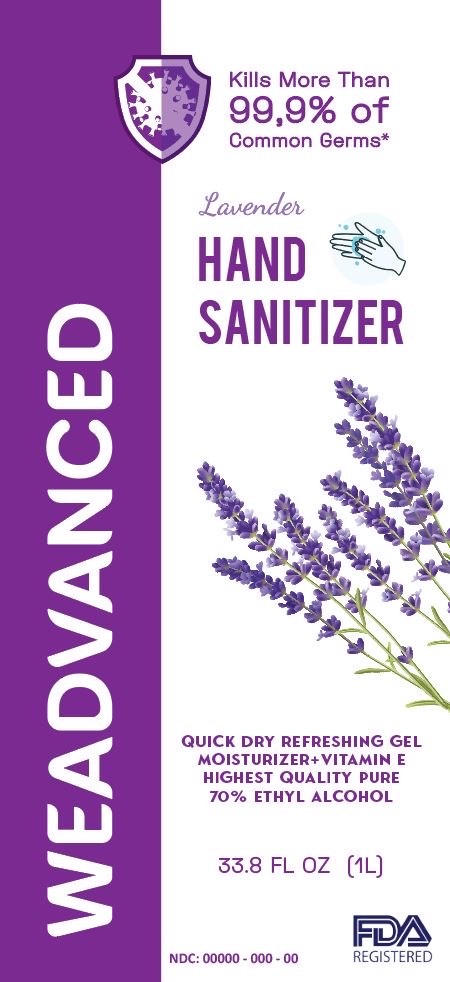 DRUG LABEL: WeAdvanced Original Hand Sanitizer
NDC: 79514-000 | Form: GEL
Manufacturer: Welog Brands LLC
Category: otc | Type: HUMAN OTC DRUG LABEL
Date: 20211222

ACTIVE INGREDIENTS: ALCOHOL 72 mL/1000 mL
INACTIVE INGREDIENTS: WATER 26.4 mL/1000 mL; GLYCERIN 0.5 mL/1000 mL; .ALPHA.-TOCOPHEROL ACETATE 0.1 mL/1000 mL; TROLAMINE 0.1 mL/1000 mL; ISOPROPYL MYRISTATE 0.5 mL/1000 mL; CARBOMER INTERPOLYMER TYPE A (ALLYL SUCROSE CROSSLINKED) 0.4 mL/1000 mL

WeAdvanced Hand Sanitizer

Drug Facts Active Ingredient(s)

Ethyl Alcohol 70% v/v

Purpose

Antimicrobial

USES

To decrease bacteria on the skin that cause disease

Recommendation

Recommended: repeated use when soap and water is not available.

Warnings

Flammable. Keep away from heat or flame. For external use only: hands.

When using this product

Do not use in or near the eyes. In case of contact rinse eyes throughly with water.

Do not use

- in children less than 2 months of age
- on open skin wounds

KEEP OUT OF CHILDREN

Do not swallow. If swallowed, get medical help or contact Poison Control Center

Directions

- Put enough product in you palm to cover hands and rub hands together briskly until dry

Children :

- Under 6 years of age should be supervised when using WEADVANCED.

Inactive ingredients

Osmosis water, Isopropyl Myristate, Glyserine, Tocopheryl Acetate, Acrylates/C10-30 Alkyl Acrylatecrosspolymer

Other Information

Store below 110F. Harmful to wood finishes and plastics. May discolor some fabrics.

QUESTIONS

Email us at Info@welogtrading.com

Package Label - Principal Display Panel

33.8 Oz / 1000ml 79514-000-000

33.8 oz / 1000ml 79514-000-000

33.8 / 1000ml 79514-001

33.8 / 1000ml 79514-001

12x1000ml carton 79514-000 / 79514-001

2x 1000ml 79514-000 / 79514-001